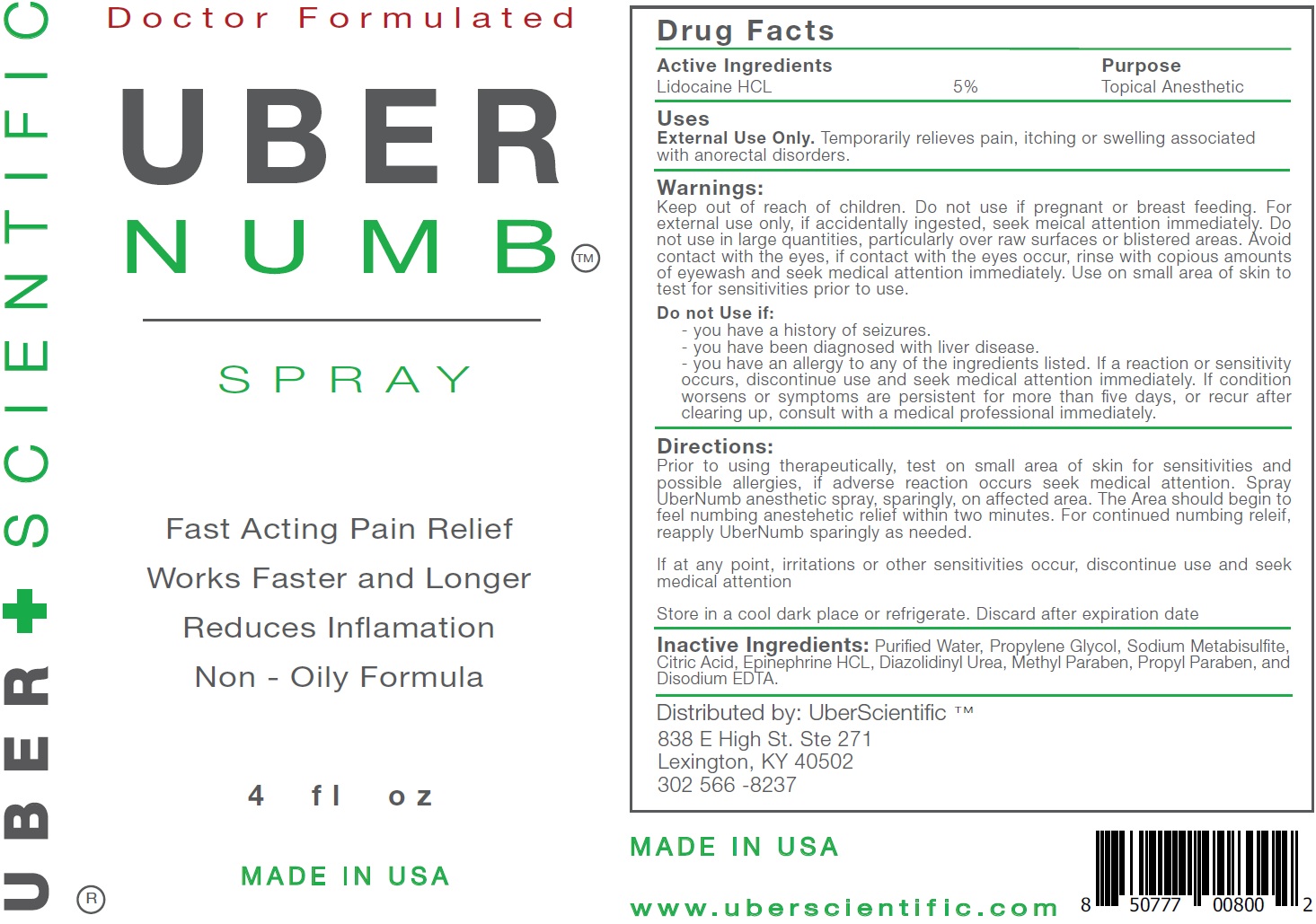 DRUG LABEL: Uber Numb
NDC: 71131-050 | Form: LIQUID
Manufacturer: UBERScientific, LLC
Category: otc | Type: HUMAN OTC DRUG LABEL
Date: 20231110

ACTIVE INGREDIENTS: LIDOCAINE HYDROCHLORIDE 50 mg/1 mL
INACTIVE INGREDIENTS: WATER; PROPYLENE GLYCOL; SODIUM METABISULFITE; CITRIC ACID MONOHYDRATE; EPINEPHRINE HYDROCHLORIDE; DIAZOLIDINYL UREA; METHYLPARABEN; PROPYLPARABEN; EDETATE DISODIUM ANHYDROUS

Uber Numb Spray

Active Ingredients

Lidocaine HCL 5%

Purpose

Topical Anesthetic

Uses

Temporarily relieves pain, itching or swelling associated with anorectal disorders. External Use Only.

Warnings:

Keep out of reach of children.

Do not use if pregnant or breast feeding. For external use only, if accidentally ingested, seek meical attention immediately. Do not use in large quantities, particularly over raw surfaces or blistered areas. Avoid contact with the eyes, if contact with the eyes occur, rinse with copious amounts of eyewash and seek medical attention immediately. Use on small area of skin to test for sensitivities prior to use.

Do not Use if:

- you have a history of seizures.
- you have been diagnosed with liver disease.
- you have an allergy to any of the ingredients listed. If a reaction or sensitivity occurs, discontinue use and seek medical attention immediately. If condition worsens or symptoms are persistent for more than five days, or recur after clearing up, consult with a medical professional immediately.

Directions:

Prior to using therapeutically, test on small area of skin for sensitivities and possible allergies, if adverse reaction occurs seek medical attention. Spray UberNumb anesthetic spray, sparingly, on affected area. The Area should begin to feel numbing anestehetic relief within two minutes. For continued numbing releif, reapply UberNumb sparingly as needed. If at any point, irritations or other sensitivities occur, discontinue use and seek medical attention Store in a cool dark place or refrigerate. Discard after expiration date

Inactive Ingredients:

Purified Water, Propylene Glycol, Sodium Metabisulfite, Citric Acid, Epinephrine HCL, Diazolidinyl Urea, Methyl Paraben, Propyl Paraben, and Disodium EDTA.

Distributed by:

UberScientific TM 838 E High St. Ste 271 Lexington, KY 40502 302 566 -8237